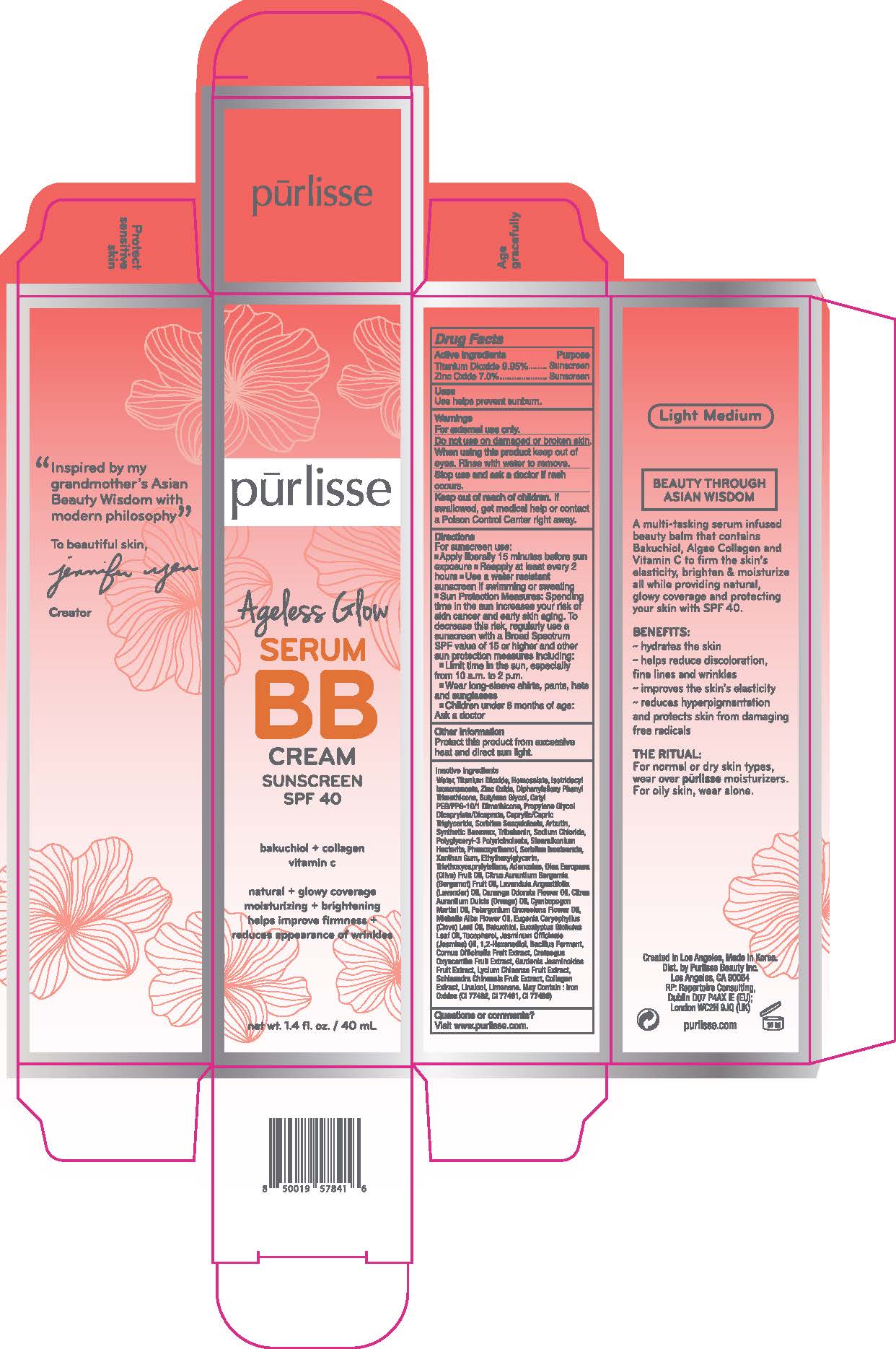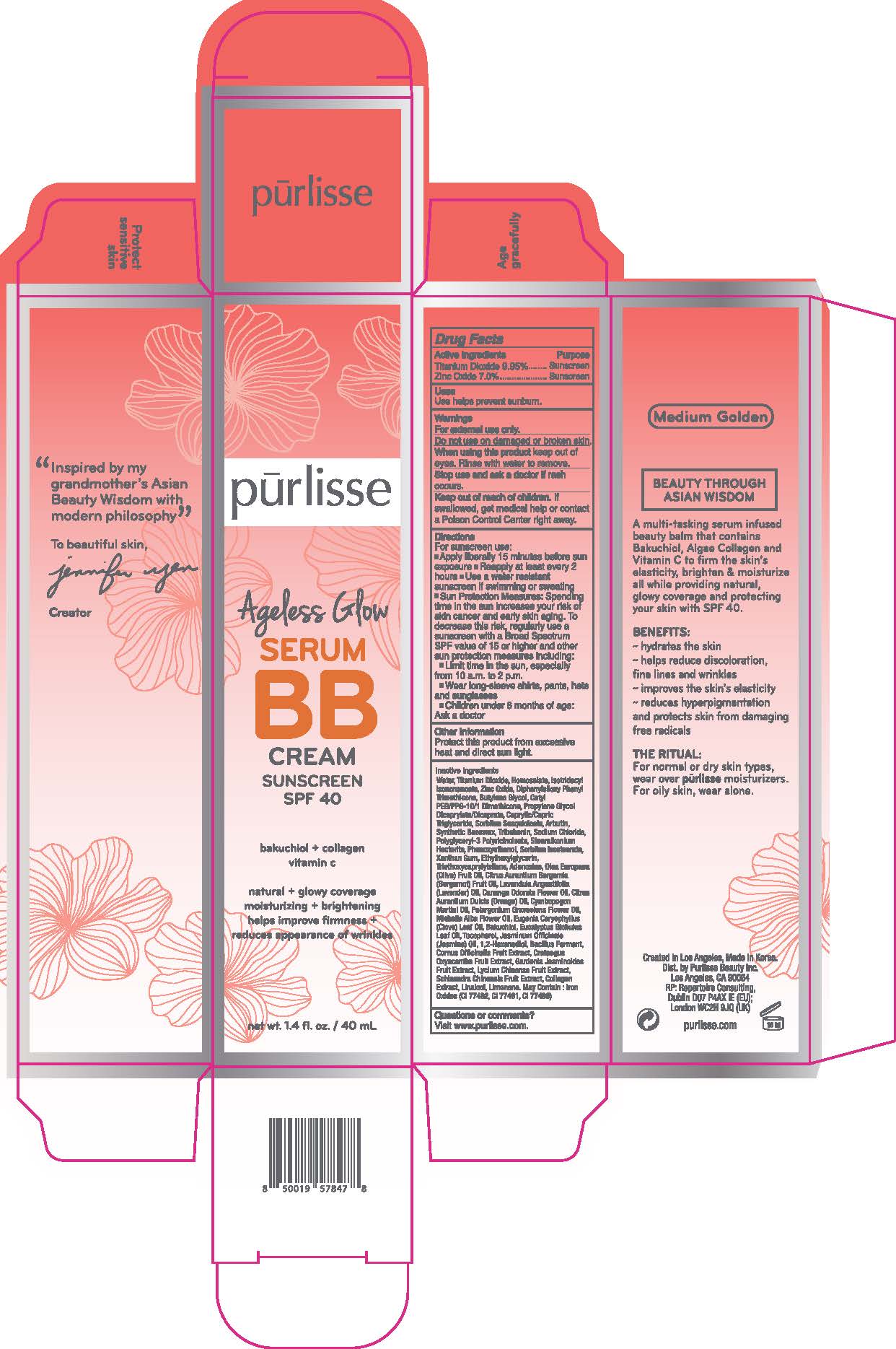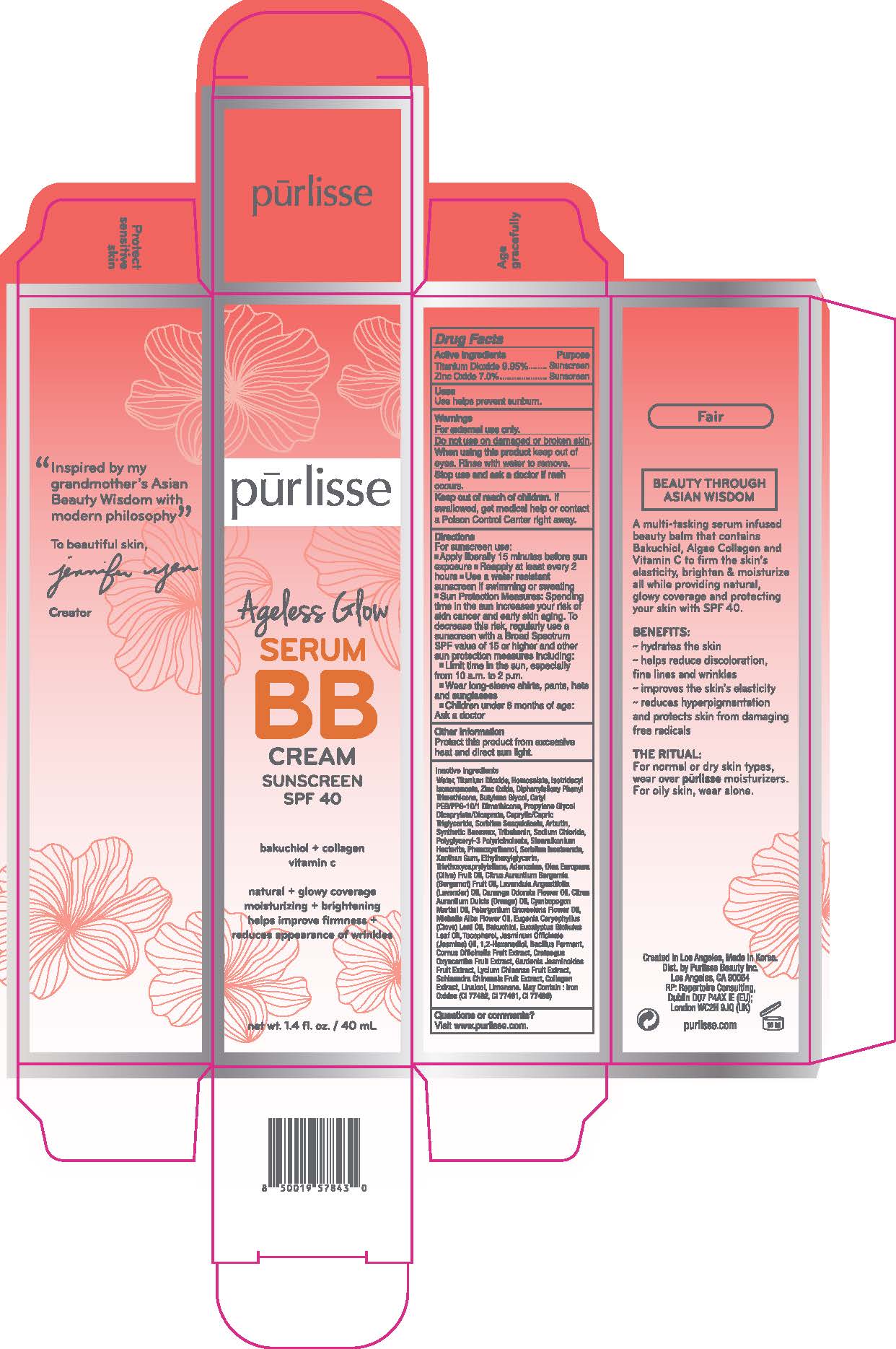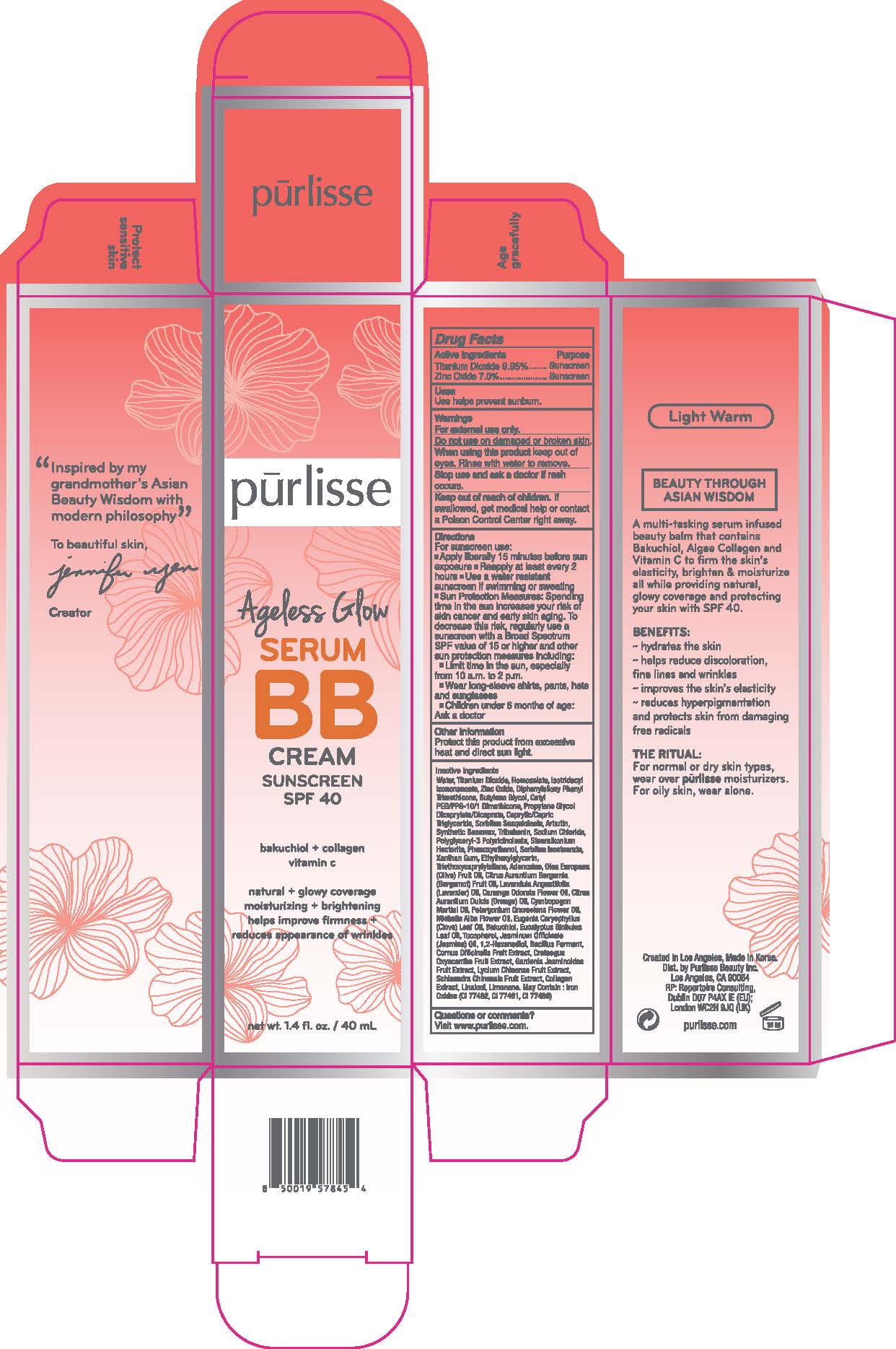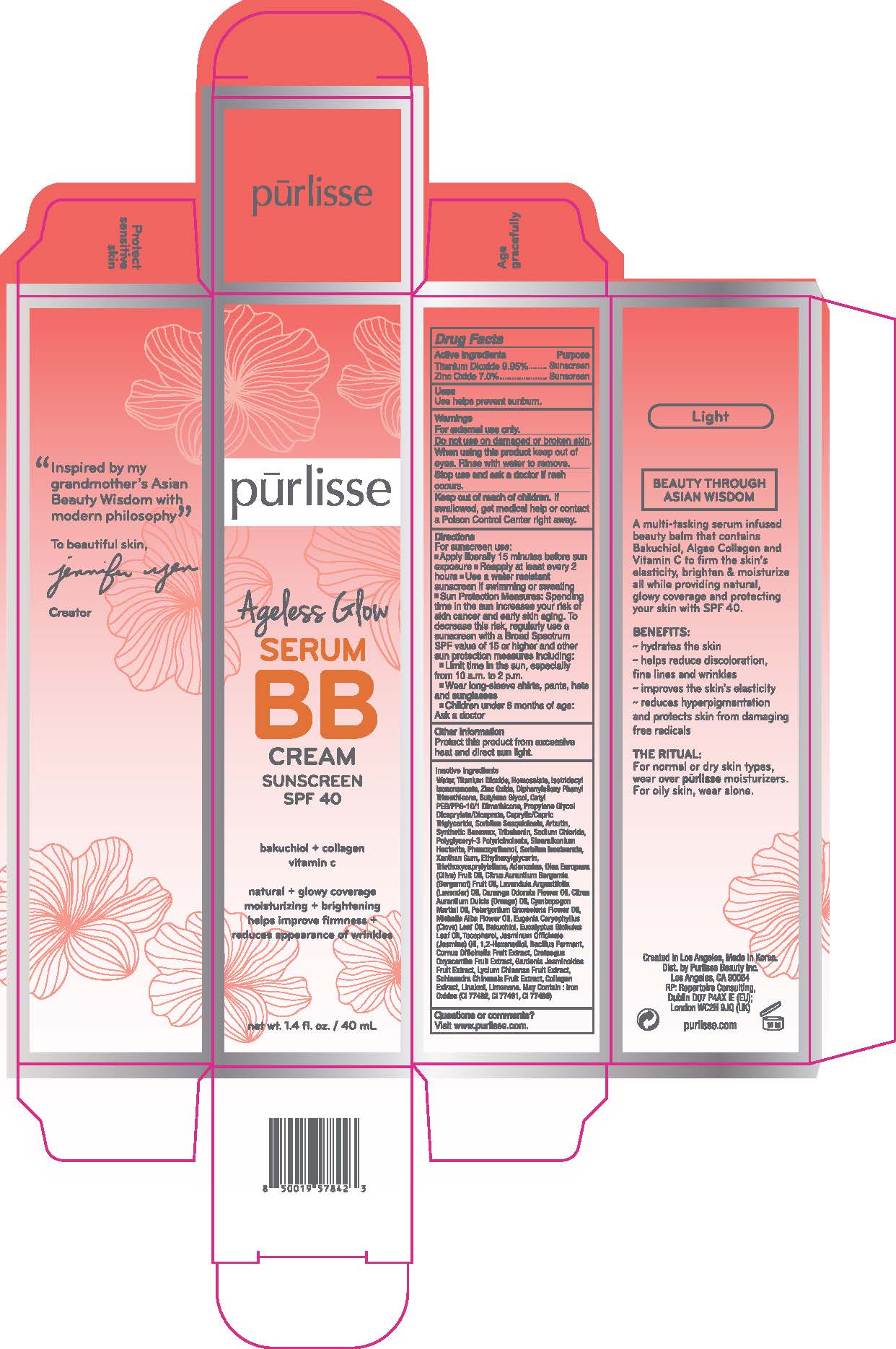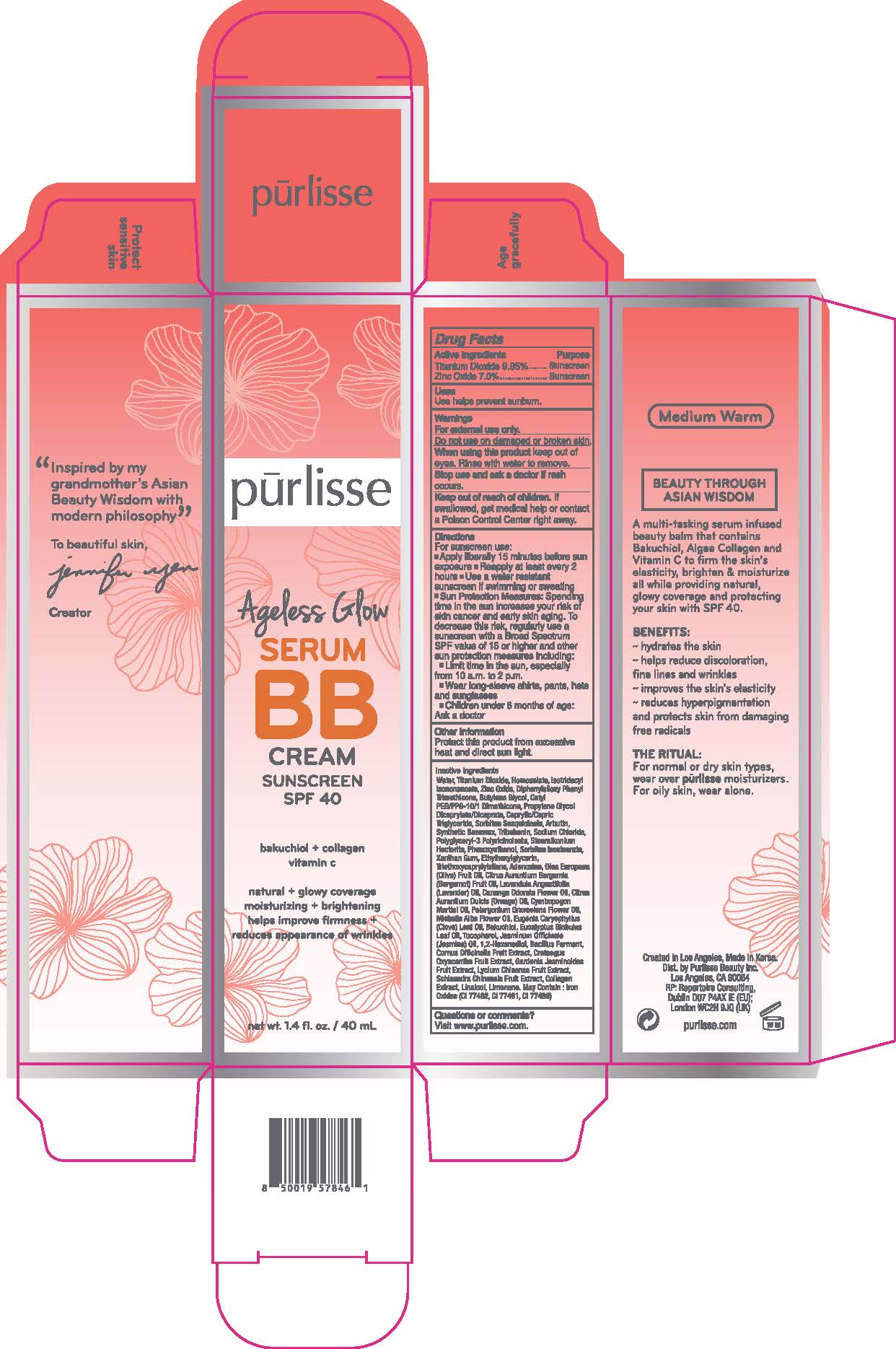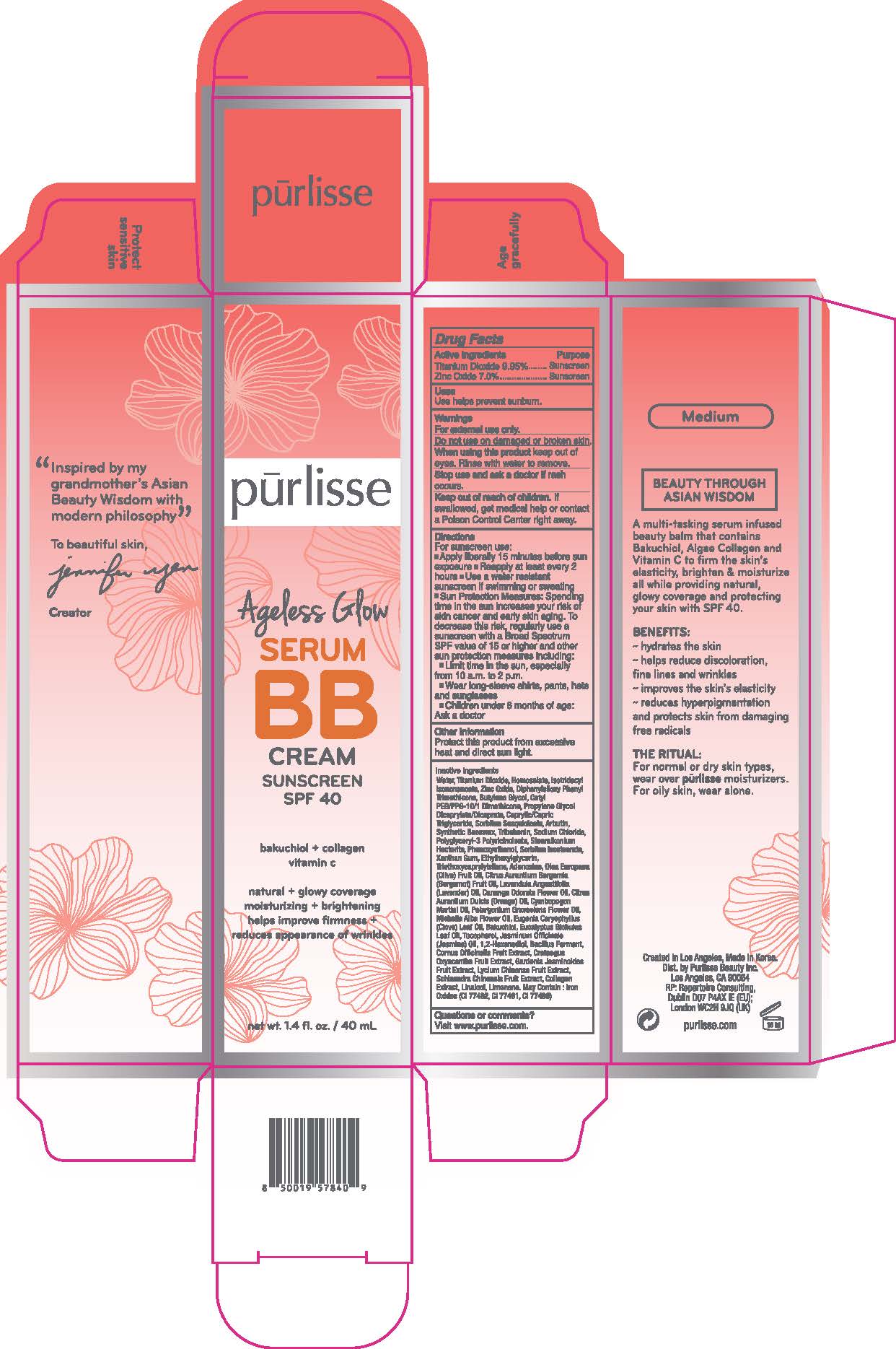 DRUG LABEL: Ageless Glow Serum BB Cream Sunscreen SPF 40 - Medium Golden
NDC: 72407-426 | Form: CREAM
Manufacturer: Pur-lisse Beauty, LLC
Category: otc | Type: HUMAN OTC DRUG LABEL
Date: 20251230

ACTIVE INGREDIENTS: HOMOSALATE 9.5 g/100 mL; TITANIUM DIOXIDE 9.95 g/100 mL; ZINC OXIDE 7 g/100 mL
INACTIVE INGREDIENTS: BUTYLENE GLYCOL; CAPRYLIC/CAPRIC TRIGLYCERIDE; SORBITAN ISOSTEARATE; OLEA EUROPAEA (OLIVE) FRUIT OIL; SCHISANDRA CHINENSIS FRUIT; ISOTRIDECYL ISONONANOATE; DIPHENYLSILOXY PHENYL TRIMETHICONE; PHENOXYETHANOL; JASMINUM OFFICINALE FLOWER; CETYL PEG/PPG-10/1 DIMETHICONE (HLB 2); ARBUTIN; CYMBOPOGON MARTINI OIL; CORNUS OFFICINALIS FRUIT; CRATAEGUS LAEVIGATA FRUIT; EUGENIA CARYOPHYLLUS (CLOVE) LEAF OIL; PROPYLENE GLYCOL DICAPRYLATE/DICAPRATE; SYNTHETIC BEESWAX; PELARGONIUM GRAVEOLENS FLOWER OIL; XANTHAN GUM; ADENOSINE; BAKUCHIOL; 1,2-HEXANEDIOL; LAVANDULA ANGUSTIFOLIA (LAVENDER) OIL; CANANGA ODORATA FLOWER OIL; CITRUS AURANTIUM DULCIS (ORANGE) OIL; MICHELIA ALBA FLOWER OIL; BACILLUS POLYFERMENTICUS; LINALOOL, (+/-)-; SODIUM CHLORIDE; STEARALKONIUM HECTORITE; GARDENIA JASMINOIDES FRUIT; TOCOPHEROL; TRIETHOXYCAPRYLYLSILANE; LYCIUM CHINENSE FRUIT; WATER; ETHYLHEXYLGLYCERIN; CITRUS AURANTIUM BERGAMIA (BERGAMOT) FRUIT OIL; POLYGLYCERYL-3 PENTARICINOLEATE; LIMONENE, (+)-; SORBITAN SESQUIOLEATE; TRIBEHENIN; MARINE COLLAGEN, SOLUBLE; EUCALYPTUS GLOBULUS LEAF OIL

Drug Facts

Active Ingredients

Homosalate 9.5%

Titanium Dioxide 9.5%

Zinc Oxide 7%

Purpose

Sunscreen

Uses

Use helps prevent sunburn.

Warnings

For external use only.

Do not use on damage or broken skin.

When using this product keep out of eyes. Rinse with water to remove.

Stop use and ask a doctor if rash occurs.

Keep out of reach of children. If swallowed, get medical help or contact a Poison Control Center right away.

Directions

For sunscreen use:

- Apply liberally 15 minutes before sun exposure
- Reapply at least every 2 hours
- Use a water resistant sunscreen if swimming or sweating
- Sun Protection Measures: Spending time in the sun increases your risk of skin cancer and early skin aging. To decrease this risk, regularly use a sunscreen with a Broad Spectrum SPF value of 15 or higher and other sun protection measures including:
- Limit time in the sun, especially from 10 a.m. to 2 p.m.
- Wear long-sleeve shirts, pants, hats and sunglasses
- Children under 6 months of age: Ask a doctor

Other Information

Protect this product from excessive heat and direct sun light.

Inactive Ingredients

Water, Isotridecyl Isononanoate, Diphenylsiloxy Phenyl Trimethicone, Butylene Glycol, Cetyl PEG/PPG-10/1 Dimethicone,Propylene Glycol Dicaprylate/Dicaprate, Caprylic/Capric Triglyceride, Sorbitan Sesquioleate, Synthetic Beeswax, Arbutin, Sodium Chloride, Tribehenin, Polyglyceryl-3 Polyricinoleate, Stearalkonium Hectorite, Phenoxyethanol, Sorbitan Isostearate, Xanthan Gum, Ethylhexylglycerin, Triethoxycaprylylsilane, Adenosine, Olea Europaea (Olive) Fruit Oil, Citrus Aurantium Bergamia (Bergamot) Fruit Oil, Lavandula Angustifolia (Lavender) Oil, Cananga Odorata Flower Oil, Citrus Aurantium Dulcis (Orange) Oil, Pelargonium Graveolens Flower Oil, Cymbopogon Martini Oil, Michelia Alba Flower Oil, Eugenia Caryophyllus (Clove) Leaf Oil, Bakuchiol, Eucalyptus Globulus Leaf Oil, Tocopherol, Jasminum Officinale (Jasmine) Oil, 1,2-Hexanediol, Bacillus Ferment, Cornus Officinalis Fruit Extract, Crataegus Oxyacantha Fruit Extract, Lycium Chinense Fruit Extract, Gardenia Jasminoides Fruit Extract, Schisandra Chinensis Fruit Extract, Collagen Extract, Linalool, Limonene. May Contain: Iron Oxides (CI 77492, CI 77491, CI 77499)

Questions or comments?

Visit www.purlisse.com.

Principal Display Panel - Ageless Glow Serum BB Cream Sunscreen SPF 40 - Fair

pūrlisse

Ageless Glow

Serum

BB

CREAM

SUNSCREEN

SPF 40

bakuchiol + collagen

vitamin c

natural + glowy coverage

moisturizing + brightening

helps improve firmness +

reduces appearance of

wrinkles

1.4 fl. oz. / 40 mL

Principal Display Panel - Ageless Glow Serum BB Cream Sunscreen SPF 40 - Light

pūrlisse

Ageless Glow

Serum

BB

CREAM

SUNSCREEN

SPF 40

bakuchiol + collagen

vitamin c

natural + glowy coverage

moisturizing + brightening

helps improve firmness +

reduces appearance of

wrinkles

1.4 fl. oz. / 40 mL

Principal Display Panel - Ageless Glow Serum BB Cream Sunscreen SPF 40 - Light Medium

pūrlisse

Ageless Glow

Serum

BB

CREAM

SUNSCREEN

SPF 40

bakuchiol + collagen

vitamin c

natural + glowy coverage

moisturizing + brightening

helps improve firmness +

reduces appearance of

wrinkles

1.4 fl. oz. / 40 mL

Principal Display Panel - Ageless Glow Serum BB Cream Sunscreen SPF 40 - Light Warm

pūrlisse

Ageless Glow

Serum

BB

CREAM

SUNSCREEN

SPF 40

bakuchiol + collagen

vitamin c

natural + glowy coverage

moisturizing + brightening

helps improve firmness +

reduces appearance of

wrinkles

1.4 fl. oz. / 40 mL

Principal Display Panel - Ageless Glow Serum BB Cream Sunscreen SPF 40 - Medium

pūrlisse

Ageless Glow

Serum

BB

CREAM

SUNSCREEN

SPF 40

bakuchiol + collagen

vitamin c

natural + glowy coverage

moisturizing + brightening

helps improve firmness +

reduces appearance of

wrinkles

1.4 fl. oz. / 40 mL

Principal Display Panel - Ageless Glow Serum BB Cream Sunscreen SPF 40 - Medium Warm

pūrlisse

Ageless Glow

Serum

BB

CREAM

SUNSCREEN

SPF 40

bakuchiol + collagen

vitamin c

natural + glowy coverage

moisturizing + brightening

helps improve firmness +

reduces appearance of

wrinkles

1.4 fl. oz. / 40 mL

Principal Display Panel - Ageless Glow Serum BB Cream Sunscreen SPF 40 - Medium Golden

pūrlisse

Ageless Glow

Serum

BB

CREAM

SUNSCREEN

SPF 40

bakuchiol + collagen

vitamin c

natural + glowy coverage

moisturizing + brightening

helps improve firmness +

reduces appearance of

wrinkles

1.4 fl. oz. / 40 mL